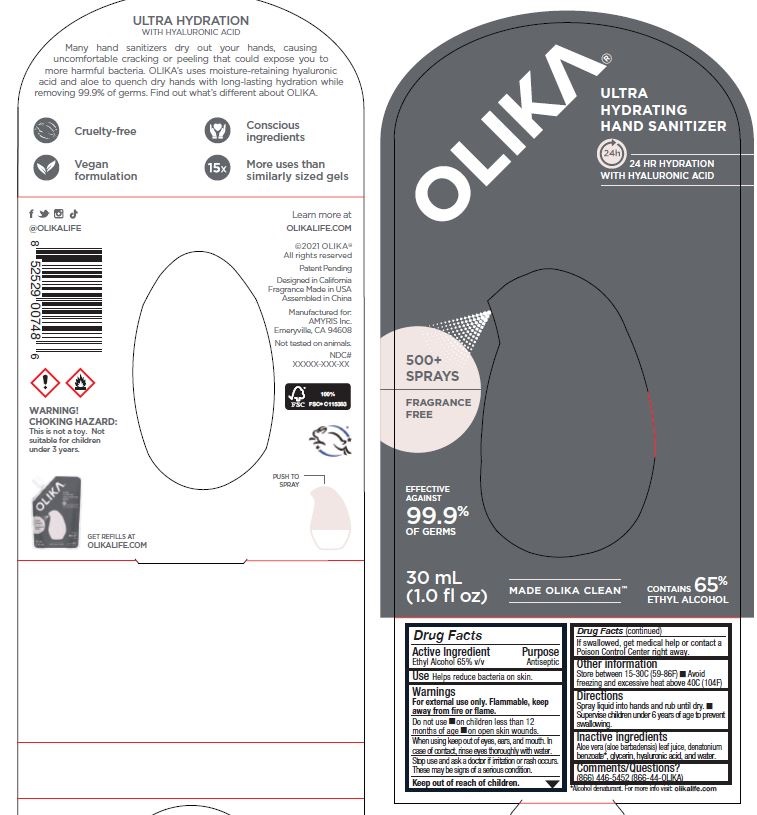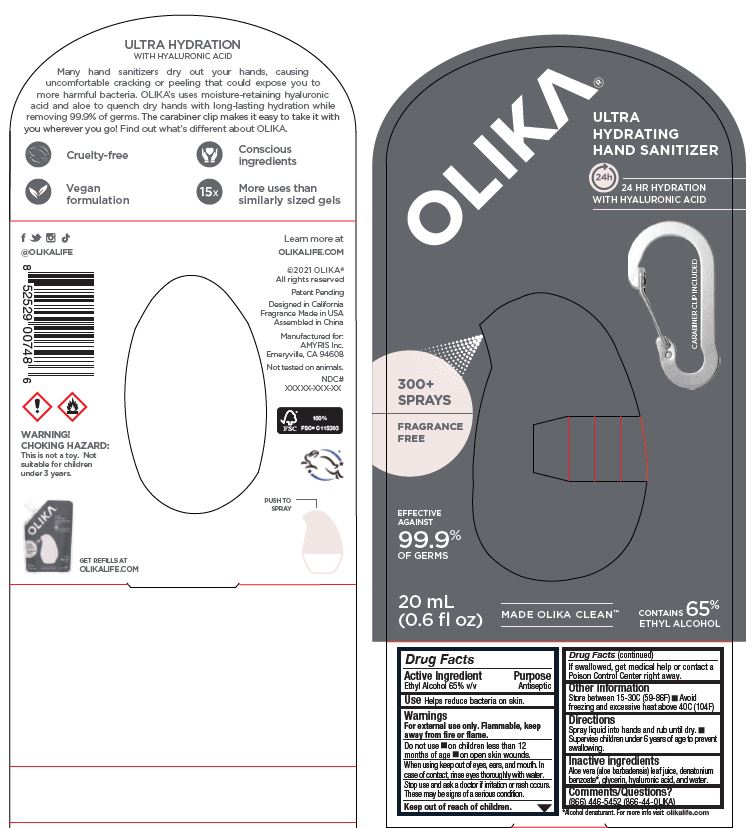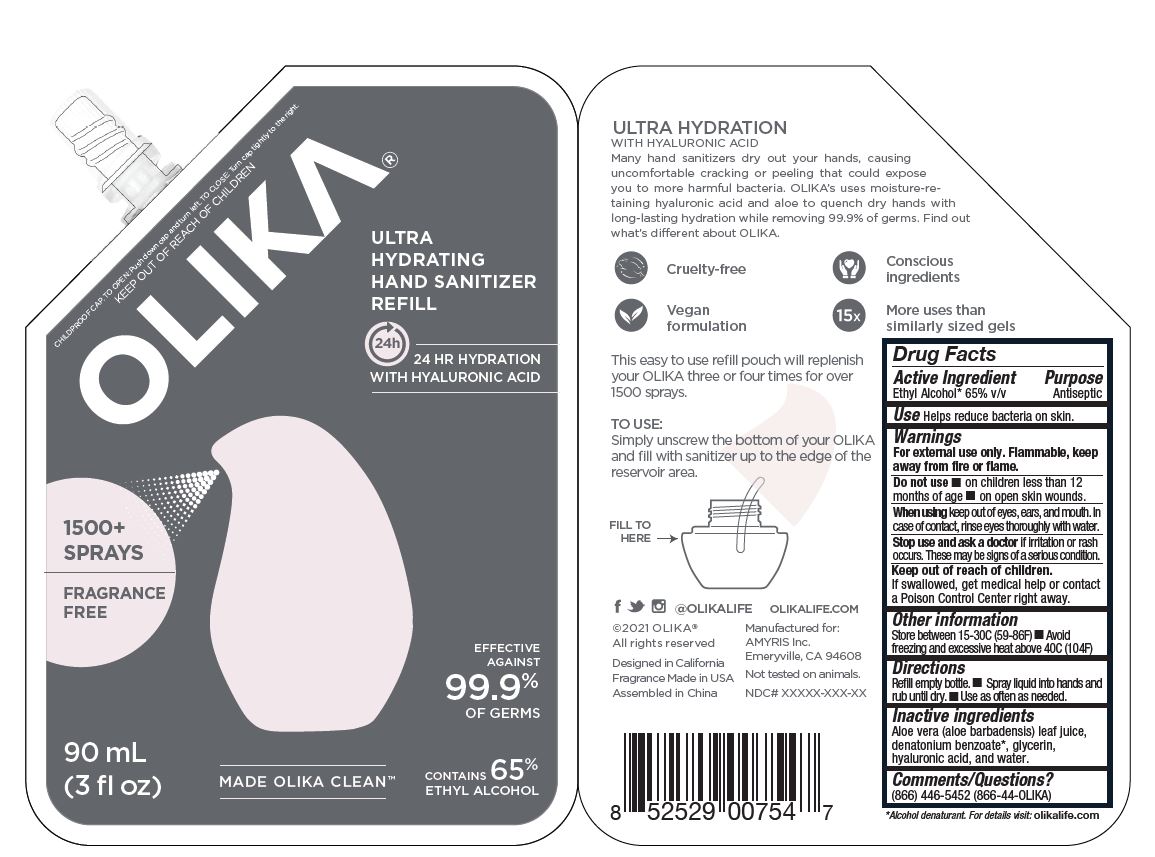 DRUG LABEL: Olika Ultra Hydrating Hand Sanitizer Fragrance Free
NDC: 73517-111 | Form: GEL
Manufacturer: Amyris, Inc
Category: otc | Type: HUMAN OTC DRUG LABEL
Date: 20230126

ACTIVE INGREDIENTS: ALCOHOL 65 mL/100 mL
INACTIVE INGREDIENTS: HYALURONATE SODIUM; GLYCERIN; ALOE VERA LEAF; WATER

Active Ingredient(s)

Alcohol 65% v/v. Purpose: Antiseptic

Purpose

Antiseptic, Hand Sanitizer

Use

Hand Sanitizer to help reduce bacteria that potentially can cause disease. For use when soap and water are not available.

Warnings

For external use only. Flammable. Keep away from heat or flame

Do not use

- in children less than 2 months of age
- on open skin wounds

When using this product keep out of eyes, ears, and mouth. In case of contact with eyes, rinse eyes thoroughly with water.
Stop use and ask a doctor if irritation or rash occurs. These may be signs of a serious condition.
Keep out of reach of children. If swallowed, get medical help or contact a Poison Control Center right away.

Stop use and ask a doctor if irritation or rash occurs. These may be signs of a serious condition.

Keep out of reach of children. If swallowed, get medical help or contact a Poison Control Center right away.

Directions

- Place enough product on hands to cover all surfaces. Rub hands together until dry.
- Supervise children under 6 years of age when using this product to avoid swallowing.

Other information

- Store between 15-30C (59-86F)
- Avoid freezing and excessive heat above 40C (104F)

Inactive ingredients

Aqua
Glycerin
Aloe Barbadensis Leaf Extract
Sodium Hyaluronate

Package Label - Principal Display Panel

Label 30 ml NDC 73517-111-01

Label 20 ml NDC 73517-111-02

Label 90 ml NDC 73517-111-03